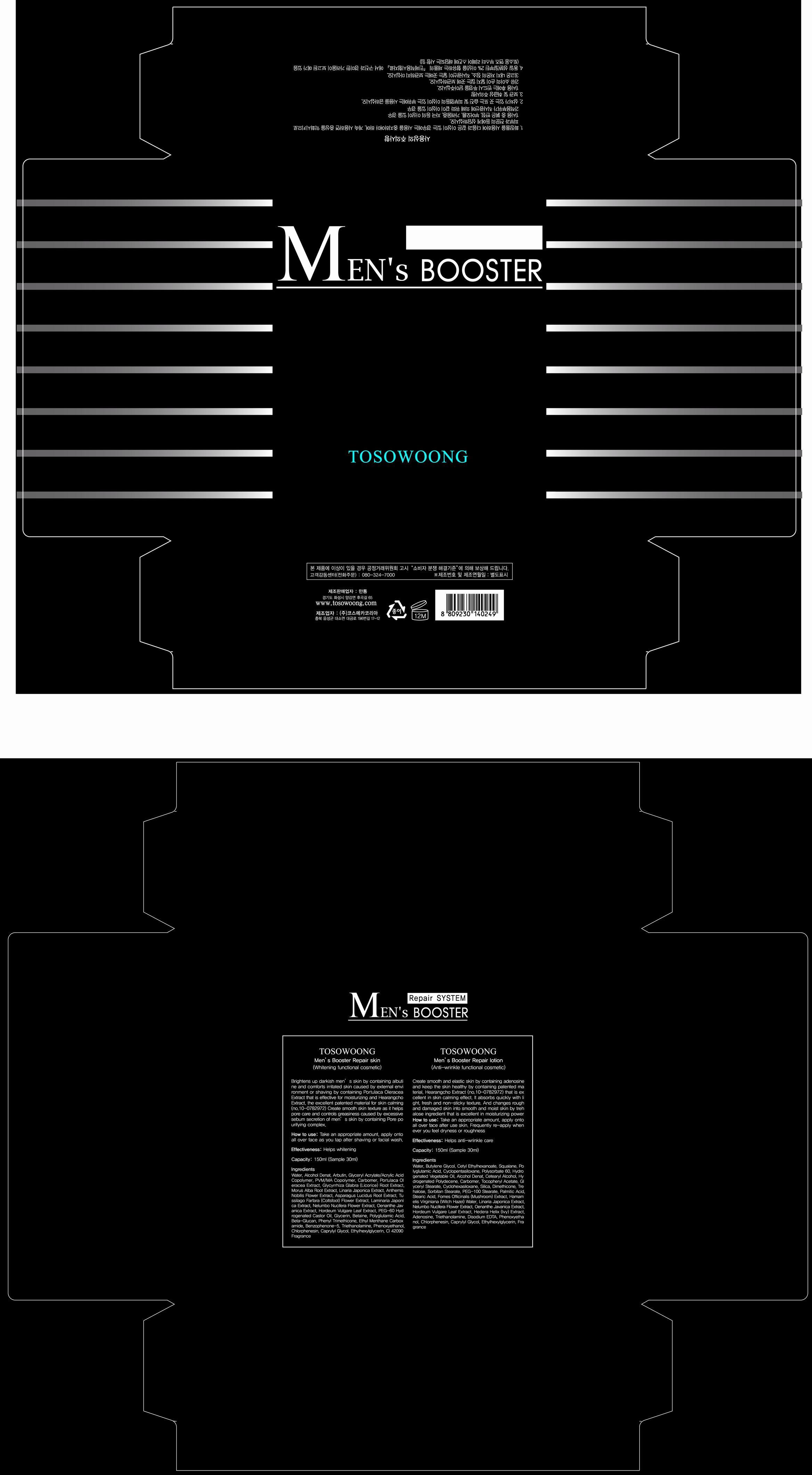 DRUG LABEL: Tosowoong Mens Booster Repair
NDC: 55249-2001 | Form: LOTION
Manufacturer: Mantong
Category: otc | Type: HUMAN OTC DRUG LABEL
Date: 20130705

ACTIVE INGREDIENTS: ADENOSINE 1 mg/150 mL
INACTIVE INGREDIENTS: WATER; ALCOHOL; CAPRYLYL GLYCOL; CETYL ETHYLHEXANOATE; SQUALENE; CYCLOMETHICONE 5; POLYSORBATE 60; HYDROGENATED POLYDECENE (550 MW); NELUMBO NUCIFERA FLOWER; .ALPHA.-TOCOPHEROL ACETATE; GLYCERYL MONOSTEARATE; CYCLOMETHICONE 6; DIMETHICONE; TREHALOSE; SORBITAN MONOSTEARATE; PEG-100 STEARATE; PHENOXYETHANOL; CHLORPHENESIN

Drug Facts

ACTIVE INGREDIENT

adenosine

INACTIVE INGREDIENT

water, alcohol, butylene glycol, cetyl ethylhexanoate, squalane, polyglutamic acid, cyclopentasiloxane, polysorbate 60, hydrogenated vegetable oil, alcohol denat, cetearyl alcohol, hydrogenated polydecene, carbomer, tocopheryl acetate, glyceryl stearate, cyclohexasiloxane, silica, dimethicone, trehalose, sorbitan stearate, peg-100 stearate, plamitic acid, stearic acid, fomes officinalis extract, witch hazel water, linaria japonica extract, nelumbo nucifera flower extract, oenanthe javanica extract, hordeum vulgare leaf extract, ivy extract, triethanolamine, disodium edta, phenoxyethanol, chlorphenesin, caprylyl glycol, ethylhexylglycerin, fragrance

PURPOSE

helps skin anti-wrinkle

keep out or reach of the children

INDICATIONS AND USAGE

take appropriate amount and apply onto all over face after shaving or facial wash

WARNINGS

avoid contact with eyes

DOSAGE AND ADMINISTRATION

for external use only